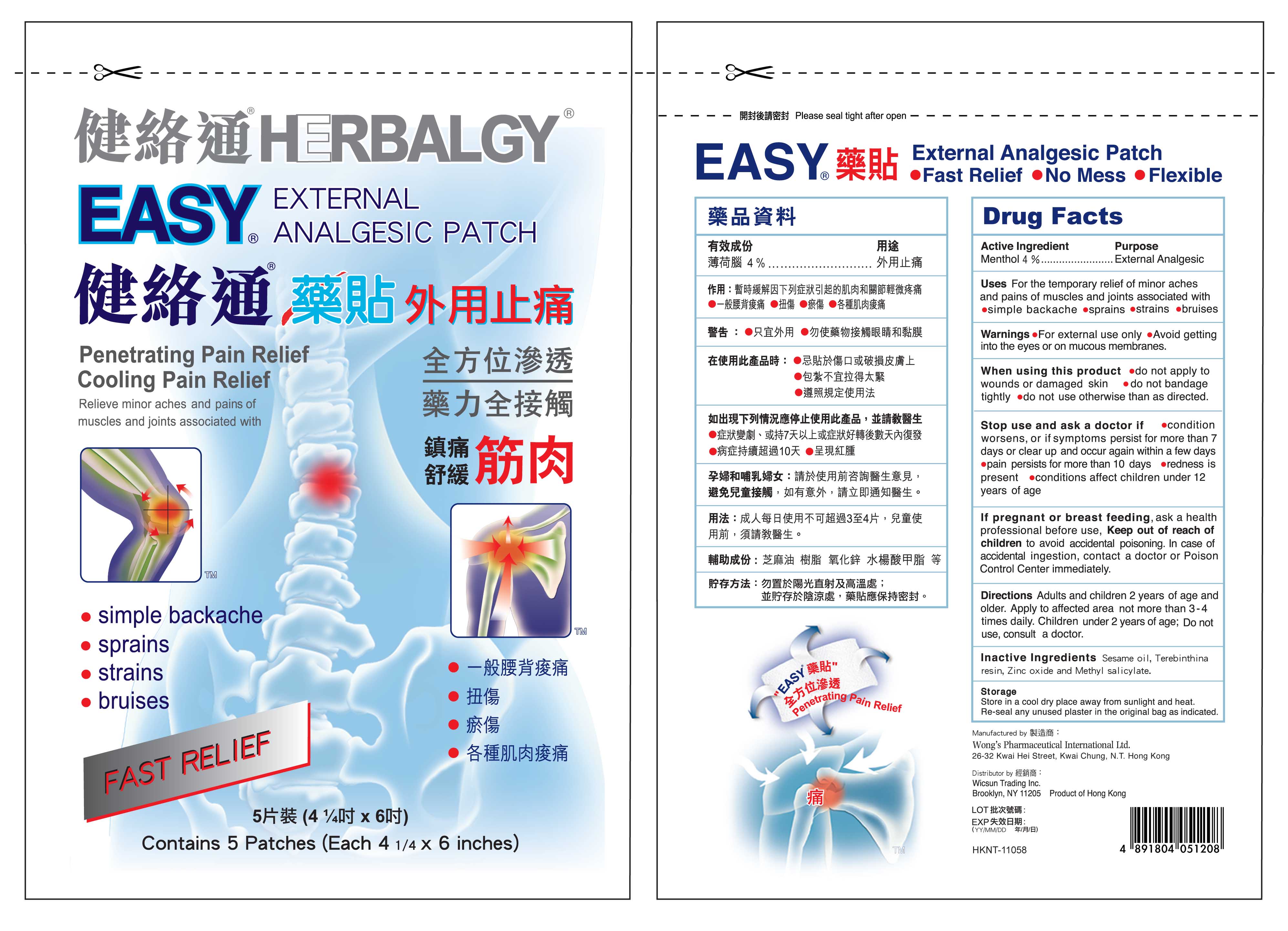 DRUG LABEL: Easy
                
NDC: 66897-002 | Form: PATCH
Manufacturer: Wicsun Trading
Category: otc | Type: HUMAN OTC DRUG LABEL
Date: 20120216

ACTIVE INGREDIENTS: Menthol 4 g/1 1
INACTIVE INGREDIENTS: SESAME OIL; SCHINUS TEREBINTHIFOLIUS WHOLE; ZINC OXIDE; METHYL SALICYLATE

Drug Facts

Active Ingredients

Menthol 4%

Purpose

External Analgesic

Uses

For the temporary relief of minor pains and aches of muscles and joints associated with:

- simple backache
- arthritis
- strains
- bruises

Warnings

- For external use only
- Avoid getting into the eyes or on mucus membranes.

When using this product

- do not apply to wound or damaged skin.
- do not bandage tightly
- do not use otherwise than as directed

Stop use and ask a doctor if

- If condition worsens, or if symptoms persist for more than 7 days or clear up and occur again within a few days.
- pain persists for more than 10 days
- redness is present
- conditions affect children under 12 years of age

PREGNANCY OR BREAST FEEDING

If pregnant or breast feeding, ask a health professional before use.

Keep out of reach of children to avoid accidental poisoning. In case of accidental ingestion, contact a doctor or Poison Control Center immediately

Directions
Adults and children2 years of age and older. Apply to affected area not more than 3-4 times daily.

Children under 2 years of age: Do not use, consult a doctor

INACTIVE INGREDIENT

Inactive Ingredients Sesame Oil, Terebinthina resin, Zinc Oxide and Methyl salicylate

Package Label